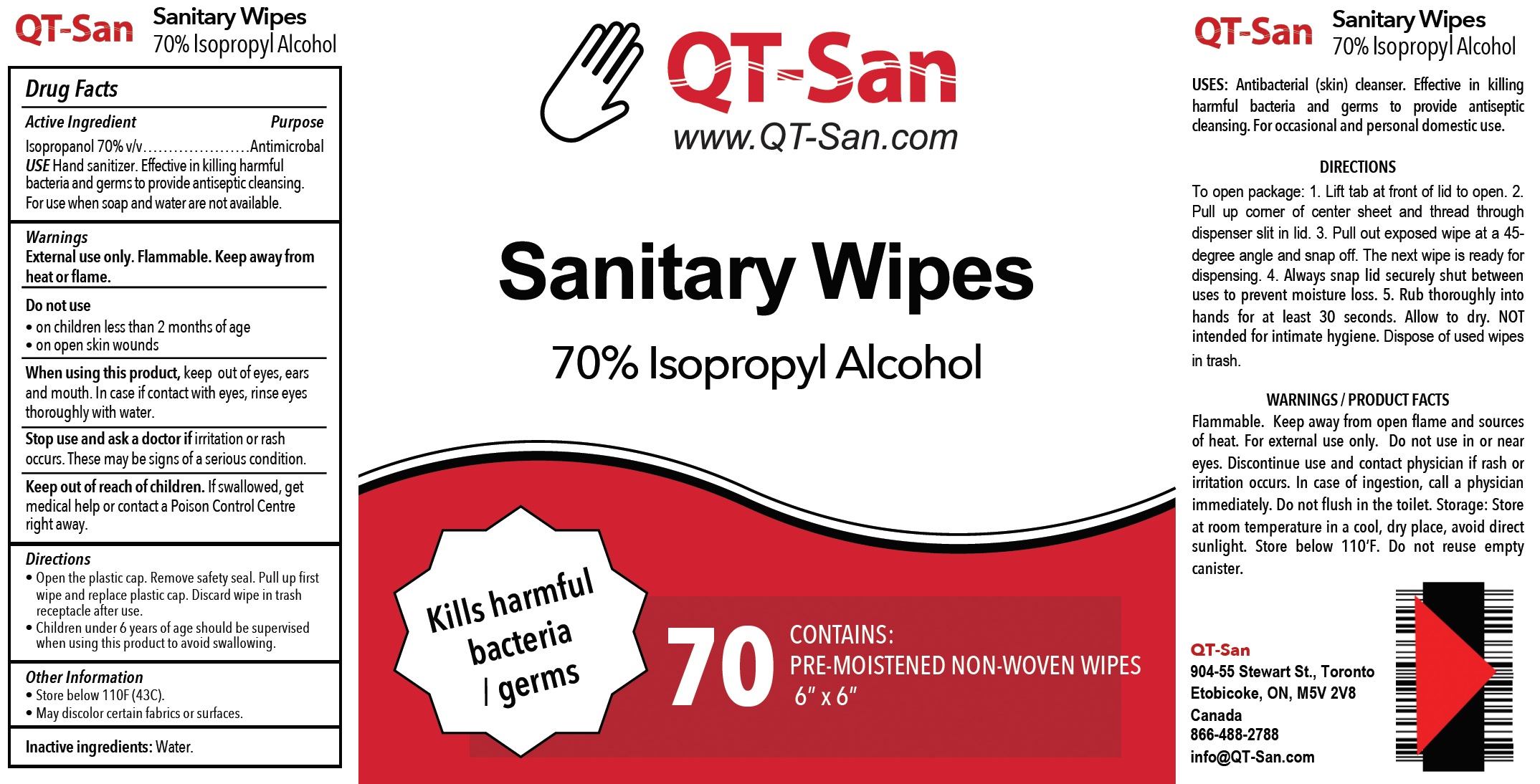 DRUG LABEL: QT-San Sanitary Wipes
NDC: 80910-001 | Form: CLOTH
Manufacturer: Royalpak Inc
Category: otc | Type: HUMAN OTC DRUG LABEL
Date: 20201102

ACTIVE INGREDIENTS: ISOPROPYL ALCOHOL 0.7 mL/1 mL
INACTIVE INGREDIENTS: WATER

QT-San Sanitary Wipes

Active Ingredient

Isopropanol 70% v/v

Purpose

Antimicrobal

USE

Hand sanitizer. Effective in killing harmful bacteria and germs to provide antiseptic cleansing. For use when soap and water are not available.

Warnings

External use only. Flammable. Keep away from heat or flame.

Do not use

• on children less than 2 months of age
• on open skin wounds

When using this product,

keep out of eyes, ears and mouth. In case if contact with eyes, rinse eyes thoroughly with water.

Stop use and ask a doctor if

irritation or rash occurs. These may be signs of a serious condition.

Keep out of reach of children.

If swallowed, get medical help or contact a Poison Control Centre right away.

Directions

- Open the plastic cap. Remove safety seal. Pull up first wipe and replace plastic cap. Discard wipe in trash receptacle after use.
- Children under 6 years of age should be supervised when using this product to avoid swallowing.

Other Information

- Store below 110F (43C).
- May discolor certain fabrics or surfaces.

Inactive ingredients:

Water.